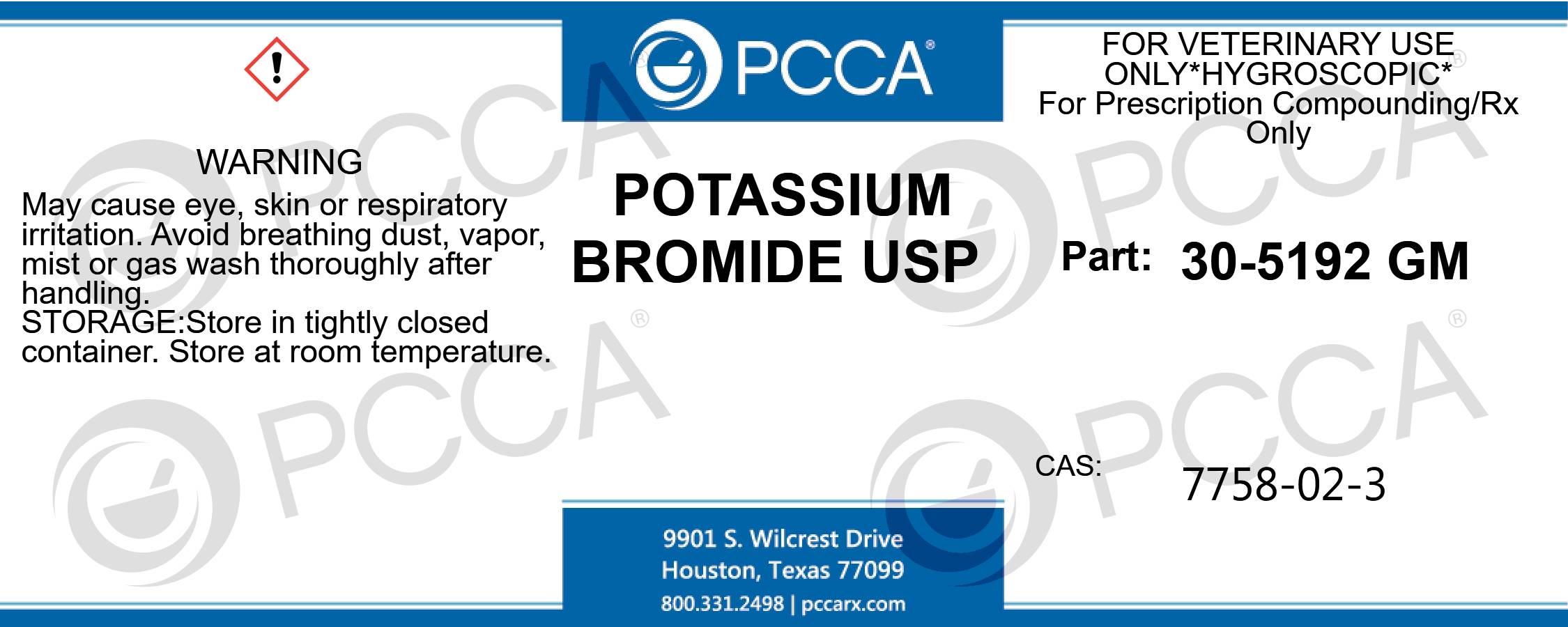 DRUG LABEL: POTASSIUM BROMIDE
NDC: 51927-5192 | Form: CRYSTAL
Manufacturer: Professional Compounding Centers of America
Category: other | Type: BULK INGREDIENT - ANIMAL DRUG
Date: 20221014

ACTIVE INGREDIENTS: POTASSIUM BROMIDE 10 kg/10 kg

30-5192 POTASSIUM BROMIDE 51927-5192-00

POTASSIUM BROMIDE USP FOR VETERINARY USE ONLY *HYGROSCOPIC* FOR PRESCRIPTION COMPOUNDING/RX ONLY PART: 30-5192 GM CAS: 7758-02-3 WARNING: MAY CAUSE EYE, SKIN OR RESPORATORY IRRITAION. AVOID BREATHING DUST, VAPOR, MIST OR GAS WASH THOROUGLY AFTERHANDLING. STORAGE: STORE IN TIGHTLY CLOSED CONTAINER. STORE AT ROOM TEMPERATURE.

POTASSIUM BROMIDE USP
FOR VETERINARY USE ONLY
*HYGROSCOPIC*
FOR PRESCRIPTION COMPOUNDING/RX ONLY
PART: 30-5192 GM
CAS: 7758-02-3
WARNING:
MAY CAUSE EYE, SKIN OR RESPORATORY IRRITAION. AVOID BREATHING DUST, VAPOR, MIST OR GAS WASH THOROUGLY AFTERHANDLING.
STORAGE: STORE IN TIGHTLY CLOSED CONTAINER. STORE AT ROOM TEMPERATURE.